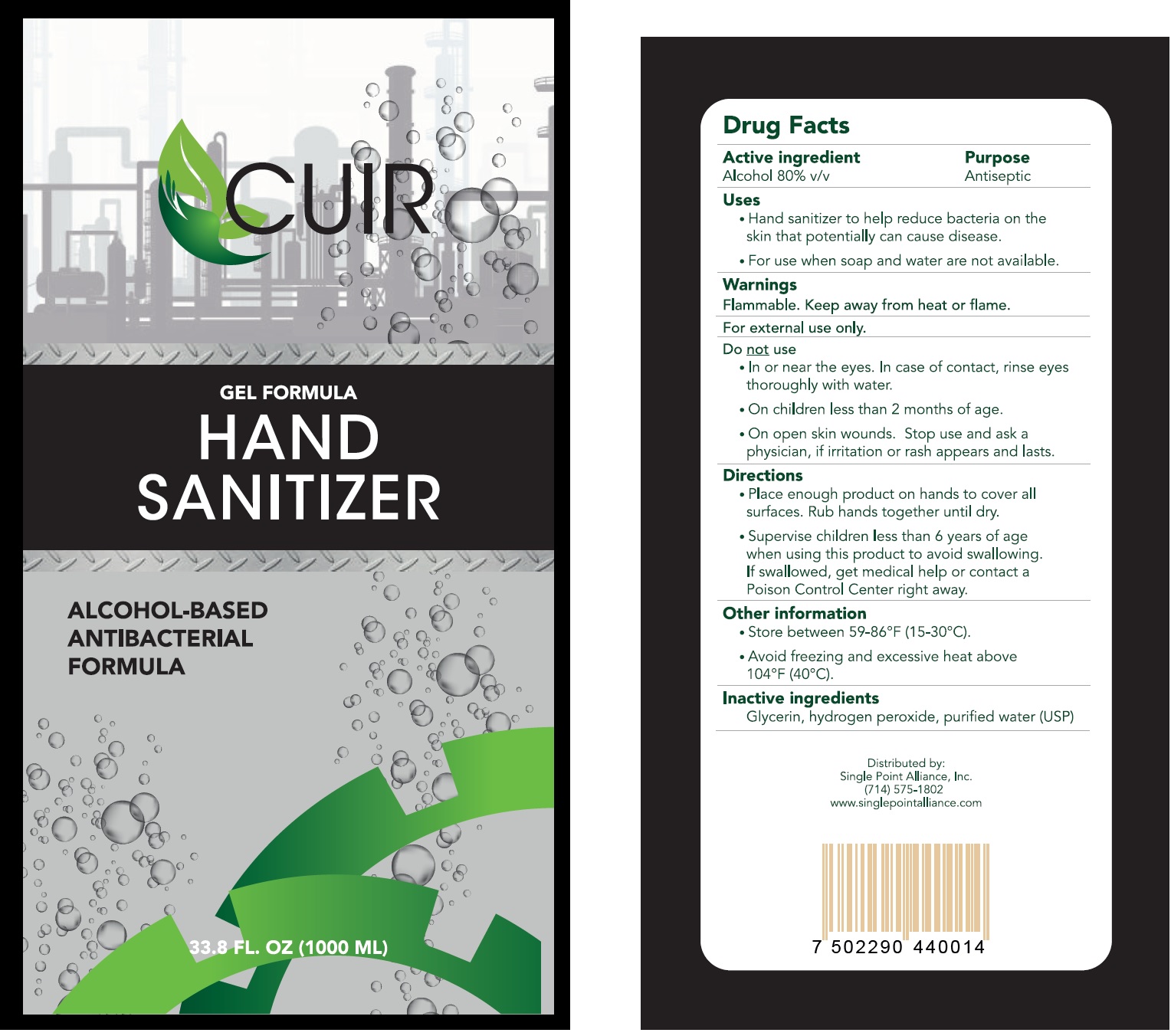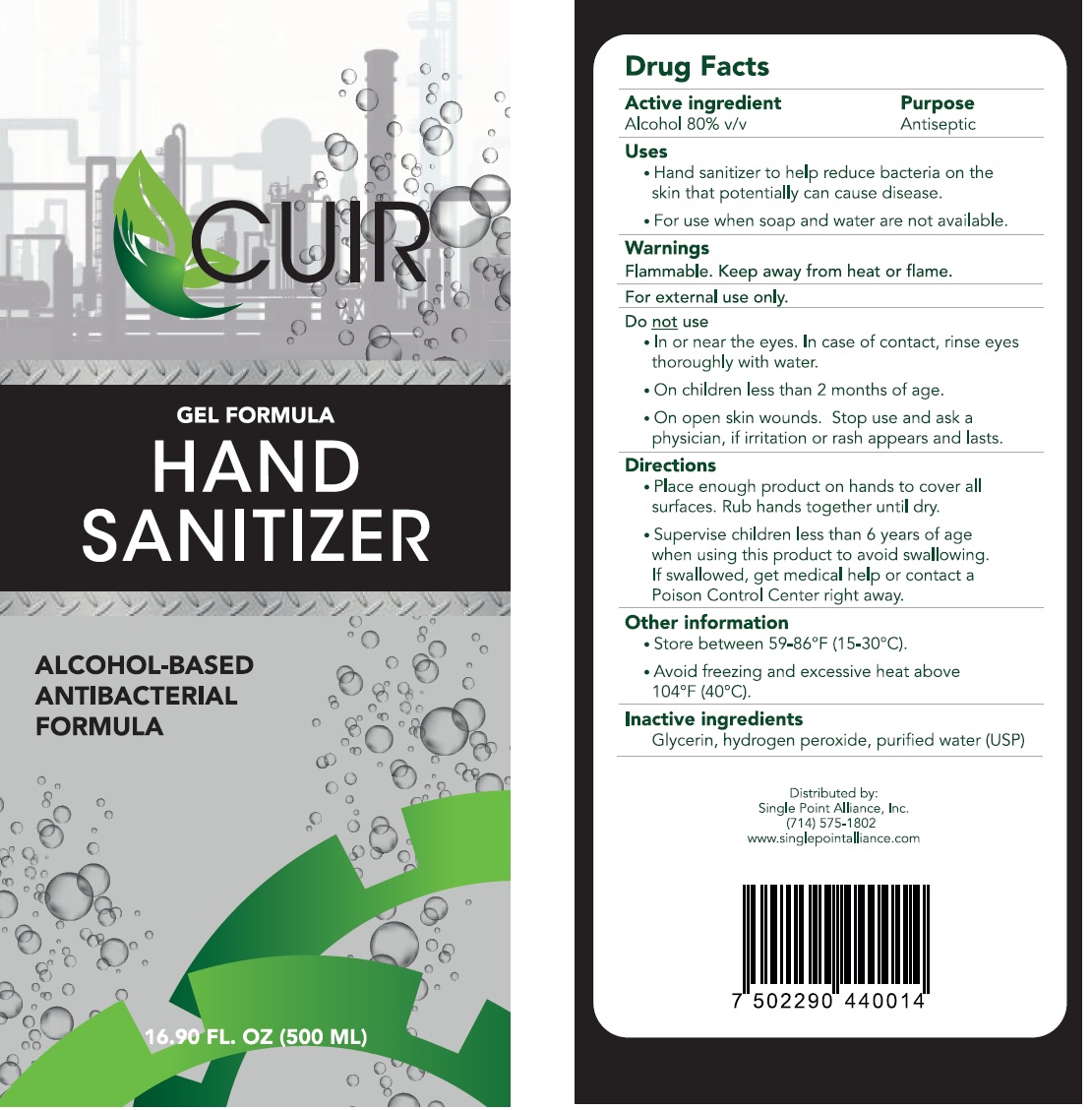 DRUG LABEL: CUIR Hand Sanitizer
NDC: 78514-001 | Form: GEL
Manufacturer: Comercial Riley S.A. de C.V.
Category: otc | Type: HUMAN OTC DRUG LABEL
Date: 20220225

ACTIVE INGREDIENTS: ALCOHOL 0.8 mL/1 mL
INACTIVE INGREDIENTS: GLYCERIN; HYDROGEN PEROXIDE; WATER

CUIR Hand Sanitizer

Active ingredient

Alcohol 80% v/v

Purpose

Antiseptic

Uses

- Hand sanitizer to help reduce bacteria on the skin that potentially can cause disease.
- For use when water soap & towel are not available.

Warnings

Flammable, Keep away from heat or flame.

For external use only.

Do not use

- In or near the eyes. In case of contact, rinse eyes thoroughly with water.
- On children less than 2 months of age.
- On open skin wounds.

Stop use and ask a physician,

if irritation or rash appears and lasts.

Directions

- Place enough product on hands to cover all surfaces. Rub hands together until dry.

KEEP OUT OF REACH OF CHILDREN

Supervise children less than 6 years of age when using this product to avoid swallowing.
If swallowed, get medical help or contact a Poison Control Center right away.

Other information

- Store between 59-86°F (15-30°C).
- Avoid freezing and excessive heat above 104°F (40°C).

Inactive ingredients

Glycerin, hydrogen peroxide, purified water (USP)